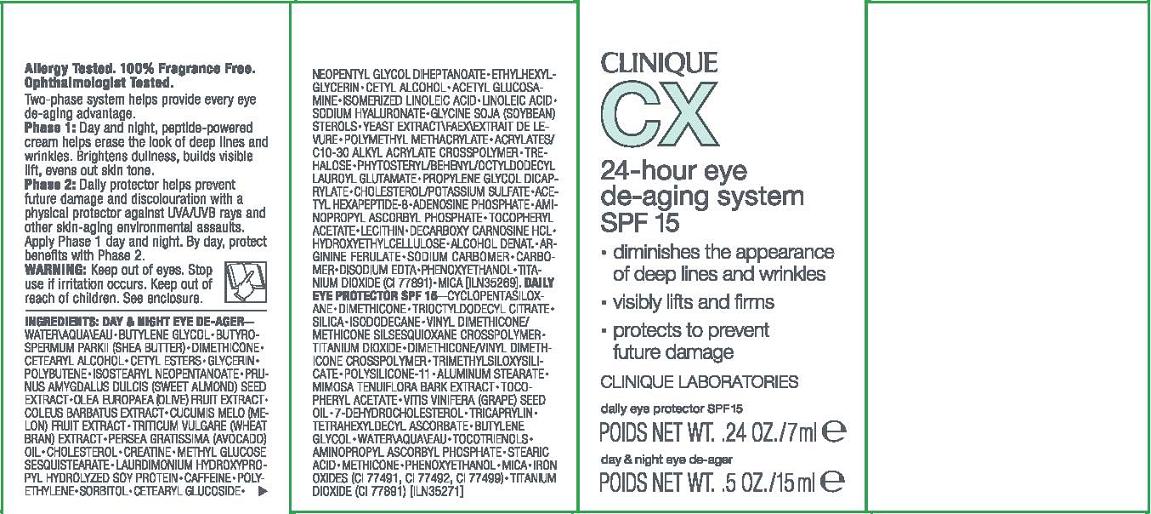 DRUG LABEL: CX DAILY EYE PROTECTOR
NDC: 49527-750 | Form: GEL
Manufacturer: CLINIQUE LABORATORIES INC
Category: otc | Type: HUMAN OTC DRUG LABEL
Date: 20110913

ACTIVE INGREDIENTS: TITANIUM DIOXIDE 7.8 mL/100 mL
INACTIVE INGREDIENTS: CYCLOMETHICONE 5; DIMETHICONE; TRICAPRYLYL CITRATE; SILICON DIOXIDE; ISODODECANE; ALUMINUM STEARATE; MIMOSA TENUIFLORA BARK; ALPHA-TOCOPHEROL ACETATE; GRAPE SEED OIL; 7-DEHYDROCHOLESTEROL; TRICAPRYLIN; TETRAHEXYLDECYL ASCORBATE; BUTYLENE GLYCOL; WATER; STEARIC ACID; PHENOXYETHANOL; MICA; FERRIC OXIDE RED

active ingredient: titanium dioxide 7.80%

INACTIVE INGREDIENT

inactive ingredients: cyclopentasiloxane [] dimethicone [] trioctyldodecyl citrate [] silica [] isododecane [] vinyl dimethicone/methicone silsesquioxane crosspolymer [] dimethicone/vinyl dimethicone crosspolymer [] trimethylsiloxysilicate [] polysilicone-11 [] aluminum stearate [] mimosa tenuiflora bark extract [] tocopheryl acetate [] vitis vinifera (grape) seed oil [] 7-dehydrocholesterol [] tricaprylin [] tetrahexyldecyl ascorbate [] butylene glycol [] water\aqua\eau [] tocotrienols [] aminopropyl ascorbyl phosphate [] stearic acid [] methicone [] phenoxyethanol [] mica [] iron oxides (ci 77491, ci 77492, ci 77499) [] titanium dioxide (ci 77891)

WARNINGS

warning: keep out of eyes. stop use if irritation occurs. keep out of reach of children

PACKAGE LABEL

PRINCIPAL DISPLAY PANEL FOR OTC SUNSCREEN PRODUCT INCLUDED IN SET. SET ALSO CONTAINS A COSMETIC PRODUCT:

CLINIQUE

CX

24 HOUR EYE DE-AGING SYSTEM

DAILY EYE PROTECTOR

SPF 15

CLINIQUE LABORATORIES, INC

NEW YORK, NY 10022